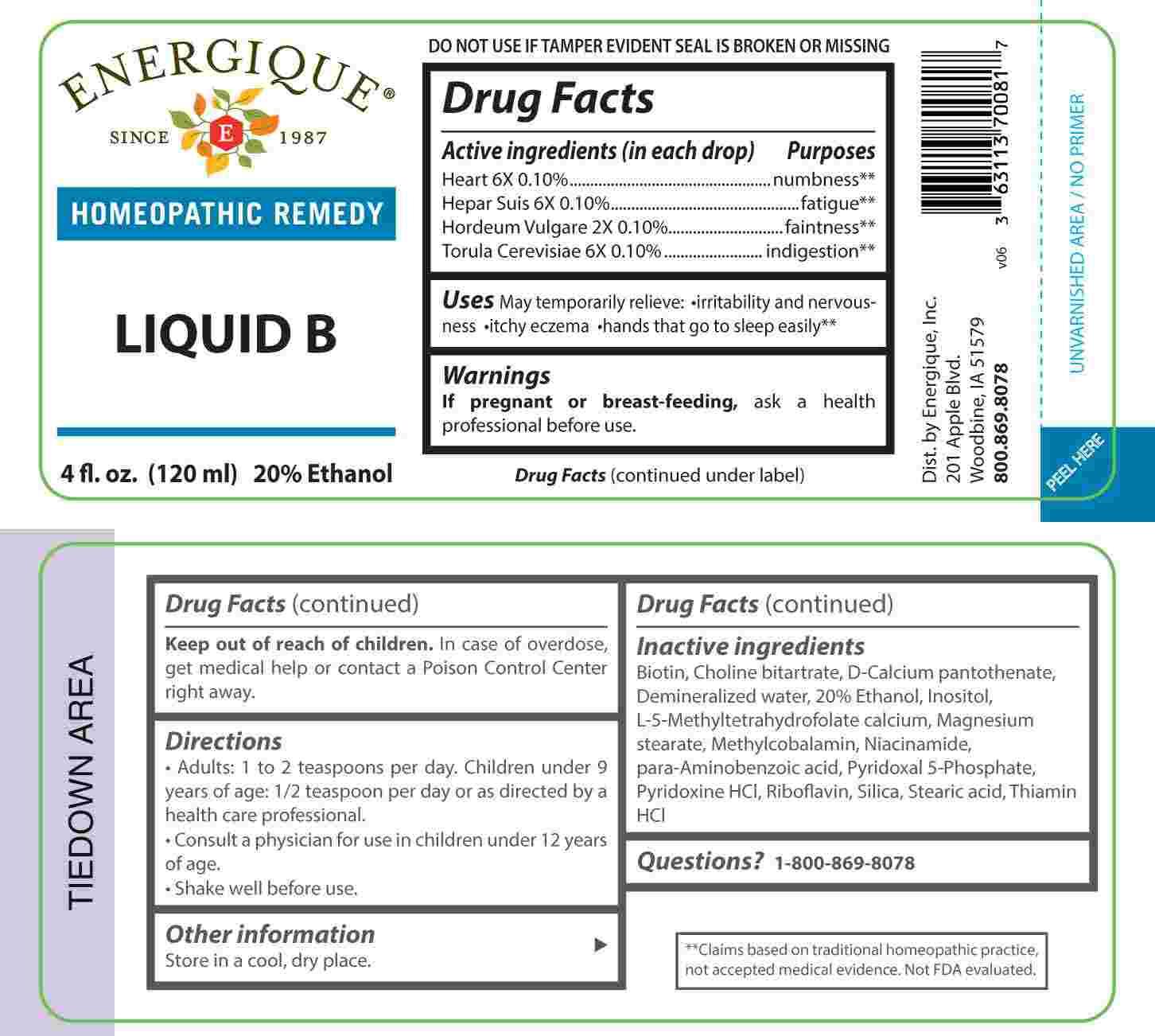 DRUG LABEL: Liquid B
NDC: 44911-0502 | Form: LIQUID
Manufacturer: Energique, Inc.
Category: homeopathic | Type: HUMAN OTC DRUG LABEL
Date: 20231206

ACTIVE INGREDIENTS: HORDEUM VULGARE TOP 2 [hp_X]/1 mL; PORK LIVER 6 [hp_X]/1 mL; PORK HEART 6 [hp_X]/1 mL; SACCHAROMYCES CEREVISIAE 6 [hp_X]/1 mL
INACTIVE INGREDIENTS: BIOTIN; CHOLINE BITARTRATE; CALCIUM PANTOTHENATE; WATER; ALCOHOL; INOSITOL; LEVOMEFOLATE CALCIUM; MAGNESIUM STEARATE; METHYLCOBALAMIN; NIACINAMIDE; AMINOBENZOIC ACID; PYRIDOXAL PHOSPHATE ANHYDROUS; PYRIDOXINE HYDROCHLORIDE; RIBOFLAVIN; SILICON DIOXIDE; STEARIC ACID; THIAMINE HYDROCHLORIDE

DRUG FACTS:

ACTIVE INGREDIENTS:

(in each tsp.): Heart 6X 0.10%, Hepar Suis 6X 0.10%, Hordeum Vulgare 2X 0.10%, Torula Cerevisiae 6X 0.10%.

PURPOSE:

Heart - numbness,** Hepar Suis - fatigue,** Hordeum Vulgare - faintness,** Torula Cerevisiae - indigestion**

**Claims based on traditional homeopathic practice, not accepted medical evidence. Not FDA evaluated.

WARNINGS:

If pregnant or breast-feeding, ask a health professional before use.

Keep out of reach of children. In case of overdose, get medical help or contact a Poison Control Center right away.

DO NOT USE IF TAMPER EVIDENT SEAL IS BROKEN OR MISSING

Store in a cool, dry place.

KEEP OUT OF REACH OF CHILDREN:

In case of overdose, get medical help or contact a Poison Control Center right away.

DIRECTIONS:

• Adults: 1 to 2 teaspoons per day. Children under 9 years of age: 1/2 teaspoon per day or as directed by a health care professional.

• Consult a physician for use in children under 12 years of age.

• Shake well before use.

USES:

May temporarily relieve: • irritability and nervousness • itchy eczema • hands that go to sleep easily.**

**Claims based on traditional homeopathic practice, not accepted medical evidence. Not FDA evaluated.

INACTIVE INGREDIENTS:

Biotin, Choline Bitartrate, D-Calcium Pantothenate, Demineralized Water, 20% Ethanol, Inositol, L-5-Methyltetrahydrofolate Calcium, Magnesium Stearate, Methylcobalamin, Niacinamide, Para Aminobenzoic Acid, Pyridoxal 5-Phosphate, Pyridoxine HCl, Riboflavin, Silica, Stearic Acid, Thiamin HCl.

QUESTIONS:

Dist. by Energique, Inc.

201 Apple Blvd.

Woodbine, IA 51579

800.869.8078

PACKAGE LABEL DISPLAY:

ENERGIQUE

SINCE 1987

HOMEOPATHIC REMEMDY

LIQUID B

4 fl. oz. (120 ml)